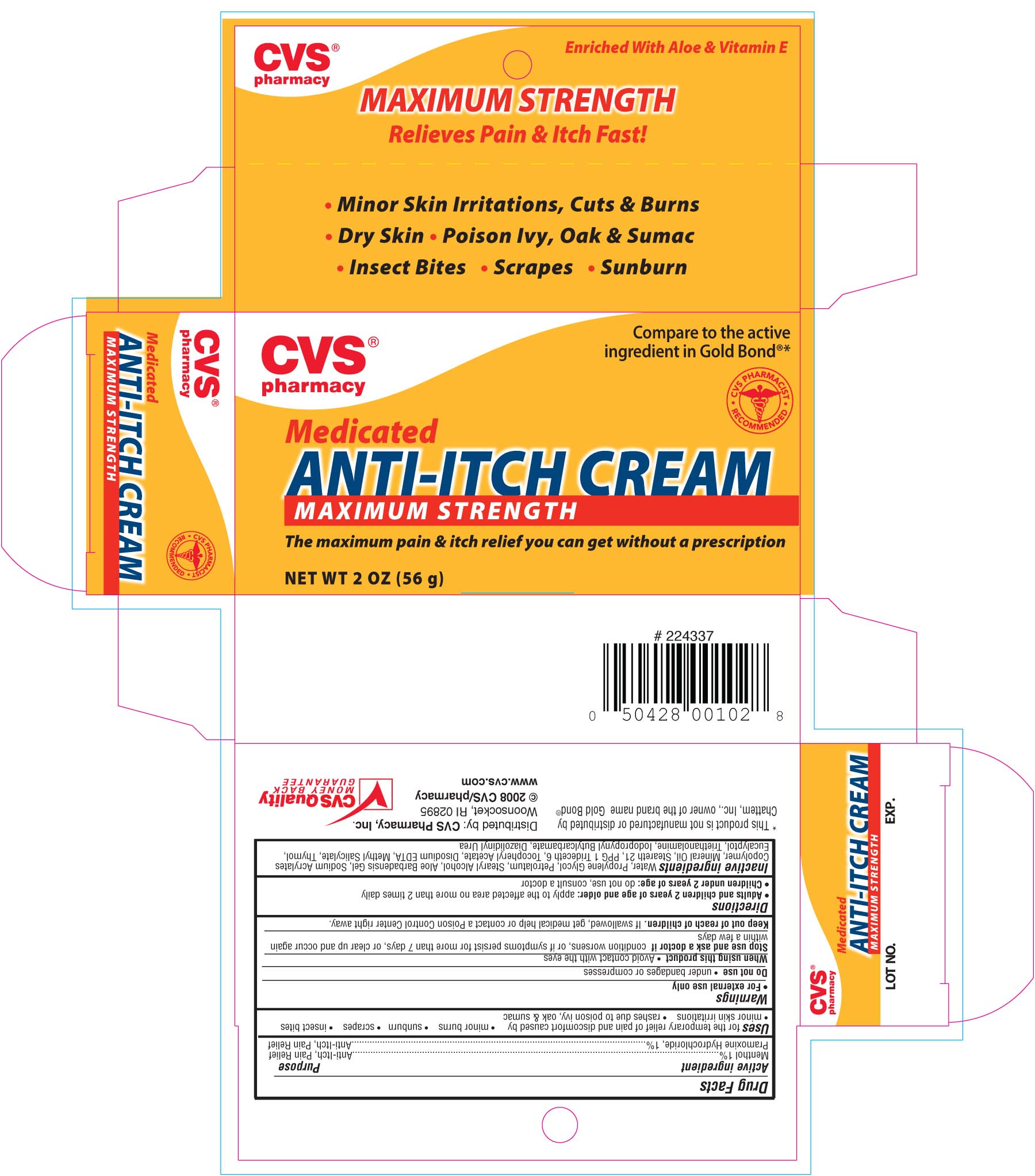 DRUG LABEL: CVS Medicated Anti-Itch 
NDC: 59779-621 | Form: CREAM
Manufacturer: CVS Pharmacy
Category: otc | Type: HUMAN OTC DRUG LABEL
Date: 20100708

ACTIVE INGREDIENTS: PRAMOXINE HYDROCHLORIDE 10 mg/1 g; MENTHOL 10 mg/1 g
INACTIVE INGREDIENTS: WATER; STEARYL ALCOHOL; PETROLATUM; PROPYLENE GLYCOL; ALOE VERA LEAF; TRIDECETH-6; STEARETH-21; STEARETH-2; THYMOL; ALPHA-TOCOPHEROL; METHYL SALICYLATE; EDETATE DISODIUM; DIAZOLIDINYL UREA; TROLAMINE; IODOPROPYNYL BUTYLCARBAMATE; PROPYLENE GLYCOL; EUCALYPTUS OIL

DRUG FACTS

Active ingredient Purpose
Menthol 1%....................................................Anti-Itch Pain Relief
Pramoxine Hydrochloride 1%............................Anti-Itch Pain Relief

Uses
For the temporary relief of pain and discomfort cause by
- minor burns - sunburn - scrapes - insect bites
- minor skin irritations - rashes due to poison ivy, oak and sumac

Keep out of reach of children. If swallowed, get medical help or contact a
Poison Control Center right away.

Uses
For the temporary relief of pain and discomfort cause by
- minor burns - sunburn - scrapes - insect bites
- minor skin irritations - rashes due to poison ivy, oak and sumac

Warnings
For external use only
Do Not use - under bandages or compresses
When using this product
- avoid contact with the eyes
Stop use and ask a doctor if condition worsens, or if symptoms persist for more than 7 days or clear up and occur again within a few days.
Keep out of reach of children.If swallowed, get medical help or contact a Poison Control Center right away.

Directions
- Adults and children 2 years and older: apply to affected area not more than 2 tim
- Children under 2 years of age: do not use, consult a doctor

Inactive Ingredients
Water, Propylene Glycol, Petrolatum, Stearyl Alcohol, Aloe Barbadensis Gel, Sodium Acrylates Copolymer, Mineral Oil, Steareth 21, PPG 1 Trideceth, 6, Toco[heryl Acetate, Disodium EDTA, Methyl Salicylate, Thymol, Eucalyptol, Triethanolamine, Iodopropynyl Butylcarbamate, Diozolidinyl Urea